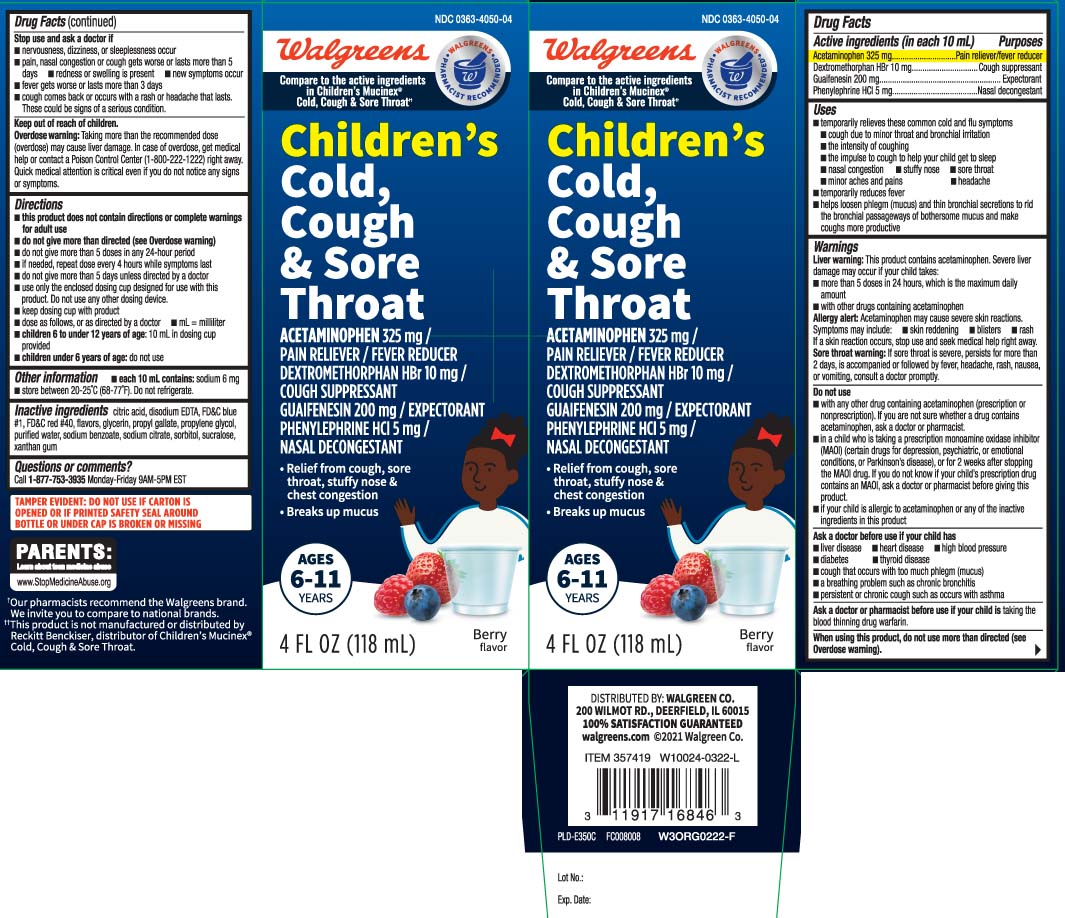 DRUG LABEL: Cough Cold and Sore Throat
NDC: 0363-4050 | Form: LIQUID
Manufacturer: Walgreens
Category: otc | Type: HUMAN OTC DRUG LABEL
Date: 20240508

ACTIVE INGREDIENTS: ACETAMINOPHEN 325 mg/10 mL; DEXTROMETHORPHAN HYDROBROMIDE 10 mg/10 mL; GUAIFENESIN 200 mg/10 mL; PHENYLEPHRINE HYDROCHLORIDE 5 mg/10 mL
INACTIVE INGREDIENTS: ANHYDROUS CITRIC ACID; EDETATE DISODIUM; FD&C BLUE NO. 1; FD&C RED NO. 40; GLYCERIN; PROPYL GALLATE; PROPYLENE GLYCOL; WATER; SODIUM BENZOATE; TRISODIUM CITRATE DIHYDRATE; SORBITOL; SUCRALOSE; XANTHAN GUM

Drug Facts

Active ingredients (in each 10 mL)

Acetaminophen 325 mg

Dextromethorphan HBr 10 mg

Guaifenesin 200 mg

Phenylephrine HCl 5 mg

Purposes

Pain reliever/fever reducer

Cough suppressant

Expectorant

Nasal decongestant

Uses

- temporarily relieves these common cold and flu symptoms:
  - cough due to minor throat and bronchial irritation
  - the intensity of coughing
  - the impulse to cough to help your child get to sleep
  - nasal congestion
  - stuffy nose
  - sore throat
  - minor aches and pains
  - headache
- temporarily reduces fever
- helps loosen phlegm (mucus) and thin bronchial secretions to rid the bronchial passageways of bothersome mucus and make coughs more productive

Warnings

Liver warning: This product contains acetaminophen. Severe liver damage may occur if your child takes:

- more than 5 doses in 24 hours, which is the maximum daily amount
- with other drugs containing acetaminophen

Allergy alert: Acetaminophen may cause severe skin reactions. Symptoms may include:

- skin reddening
- blisters
- rash

If a skin reaction occurs, stop use and seek medical help right away.

Sore throat warning: If sore throat is severe, persists for more than 2 days, is accompanied or followed by fever, headache, rash, nausea, or vomiting, consult a doctor promptly.

Do not use

- with any other drug containing acetaminophen (prescription or monprescription). If you are not sure whether a drug contains acetaminophen, ask a doctor or pharmacist.
- in a child who is taking a prescription monoamine oxidase inhibitor (MAOI) (certain drugs for depression, psychiatric, or emotional conditions, or Parkinson's disease), or for 2 weeks after stopping the MAOI drug. If you do not know if your child's prescription drug contains an MAOI, ask a doctor or pharmacist before giving this product.
- if your child is allergic to acetaminophen or any of the inactive ingredients in this product.

Ask a doctor before use if your child has

- liver disease
- heart disease
- high blood pressure
- diabetes
- thyroid disease
- cough that occurs with too much phlegm (mucus)
- a breathing problem such as chronic bronchitis
- persistent or chronic cough such as occurs with asthma

Ask a doctor or pharmacist before use if your child is

taking the blood thinning drug warfarin.

When using this product,

do not use more than directed (see Overdose warning).

Stop use and ask a doctor if

- nervousness, dizziness, or sleeplessness occur
- pain, nasal congestion or cough gets worse or lasts more than 5 days
- redness or swelling is present
- new symptoms occur
- fever gets worse or lasts more than 3 days
- cough comes back, or occurs with a rash or headache that lasts.

These could be signs of a serious condition.

Keep out of reach of children

Overdose warning: Taking more than the recommended dose (overdose) may cause liver damage. In case of overdose, get medical help or contact a Poison Control Center (1-800-222-1222) right away. Quick medical attention is critical even if you do not notice any signs or symptoms.

Directions

- this product does not contain directions or complete warnings for adult use
- do not give more than directed (see Overdose warning)
- do not give more than 5 doses in any 24-hour period
- if needed, repeat dose every 4 hours while symptoms last
- do not give more than 5 days unless directed by a doctor
- keep dosing cup with product
- use only the enclosed dosing cup designed for use with this product. Do not use any other dosing device.
- dose as follows, or as directed by a doctor
- mL=milliliter
- children 6 to under 12 years of age: 10 mL in dosing cup provided
- children under 6 years of age: do not use

Other information

- each 10 mL contains: sodium 6 mg
- store between 20-25ºC (68-77ºF). Do not refrigerate.

Inactive ingredients

anhydrous citric acid, EDTA disodium, FD&C blue #1, FD&C red #40, flavors, glycerin, propyl gallate, propylene glycol, purified water, sodium benzoate, sodium citrate dihydrate, sorbitol, sucralose, xanthan gum

Questions or comments?

Call 1-877-753-3935 Monday-Friday 9AM-5PM EST

Principal Display Panel

Compare to the active ingredients in Children's Mucinex® Cold, Cough & Sore Throat††

Children's

Cold, Cough & Sore Throat

ACETAMINOPHEN 325 mg /

PAIN RELIEVER / FEVER REDUCER

DEXTROMETHORPHAN HBr 10 mg /

COUGH SUPPRESSANT

GUAIFENESIN 200 mg / EXPECTORANT

PHENYLEPHRINE HCI 5 mg / NASAL DECONGESTANT

- Relief from cough, sore throat, stuffy nose & chest congestion
- Breaks up mucus

AGES 6 - 11 YEARS

FL OZ (mL)

Berry flavor

††This product is not manufactured or distributed by Reckitt Benckiser, distributor of Children's Mucinex® Cold, Cough & Sore Throat.

TAMPER EVIDENT: DO NOT USE IF CARTON IS OPENED OR IF PRINTED SAFETY SEAL AROUND BOTTLE OR UNDER CAP IS BROKEN OR MISSING

DISTRIBUTED BY: WALGREEN CO.

200 WILMOT RD., DEERFIELD, IL 60015

walgreens.com

Package Label

WALGREENS Children's Cold, Cough, and Sore Throat Berry Flavor